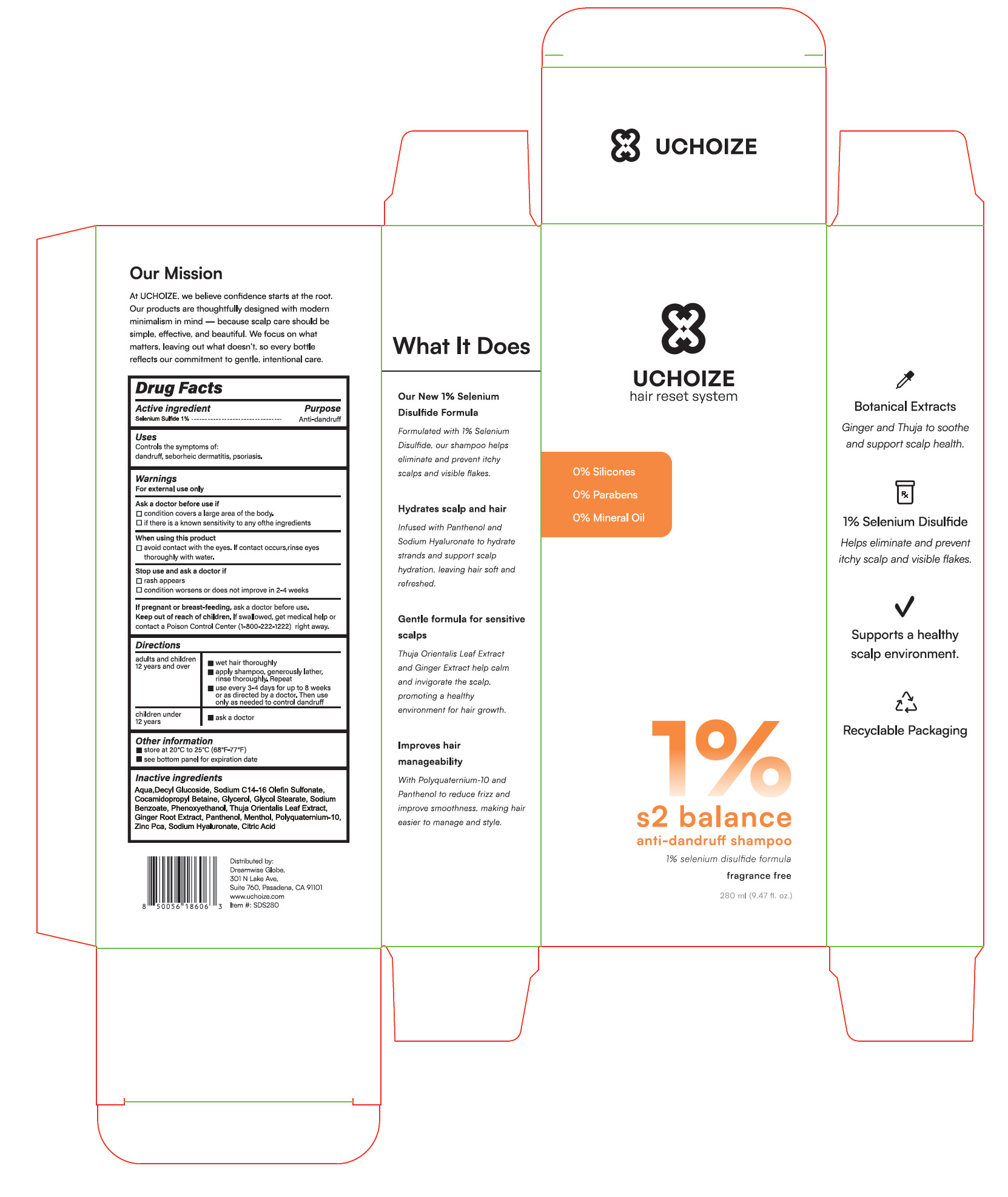 DRUG LABEL: UCHOIZE S2 Balance Anti-Dandruff
NDC: 85724-001 | Form: SHAMPOO
Manufacturer: Dreamwise International Corp
Category: otc | Type: HUMAN OTC DRUG LABEL
Date: 20250603

ACTIVE INGREDIENTS: SELENIUM SULFIDE 1 g/100 mL
INACTIVE INGREDIENTS: GINGER; MENTHOL; PANTHENOL; SODIUM HYALURONATE; POLYQUATERNIUM-10 (125 MPA.S AT 2%); ZINC PCA; ACONITIC ACID; AQUA; DECYL GLUCOSIDE; SODIUM C14-16 OLEFIN SULFONATE; COCAMIDOPROPYL BETAINE; GLYCERIN; GLYCOL STEARATE; SODIUM BENZOATE; PHENOXYETHANOL; PLATYCLADUS ORIENTALIS LEAF

85724-001

Active Ingredient(s)

Selenium Sulfide 1%

Purpose

Anti-dandruff

Use

Controls the symptoms of:
dandruff, seborheic dermatitis, psoriasis.

Warnings

For external use only

Do not use

If pregnant or breast-feeding, ask a doctor before use.

WHEN USING

avoid contact with the eyes. If contact occurs,rinse eyes
thoroughly with water,

STOP USE

rash appears
condition worsens or does not improve in 2-4 weeks

Keep out of reach of children. If swallowed, get medical help or
contact a Poison Control Center (1-800-222-1222) right away,

Directions

adults and children 12 years and over

1. wet hair thoroughly
2. apply shampoo, generously lather, rinse thoroughly. Repeat
3. use every 3-4 days for up to 8 weeks or as directed by a doctor, Then use only as needed to control dandruff

children under 12 years

1. ask a doctor

Other information

store at 20°C to 25°C (68°F-77°F)
see bottom panel for expiration date

Inactive ingredients

Aqua,DecyI Glucoside, Sodium C14-16 Olefin Sulfonate, Cocamidopropyl Betaine, Glycerol, Glycol Stearate, Sodium
Benzoate, Phenoxyethanol, Thuja Orientalis Leaf Extract, Ginger Root Extract, Panthenol, Menthol, Polyquaternium-10,
Zinc Pca, Sodium Hyaluronate, Citric Acid